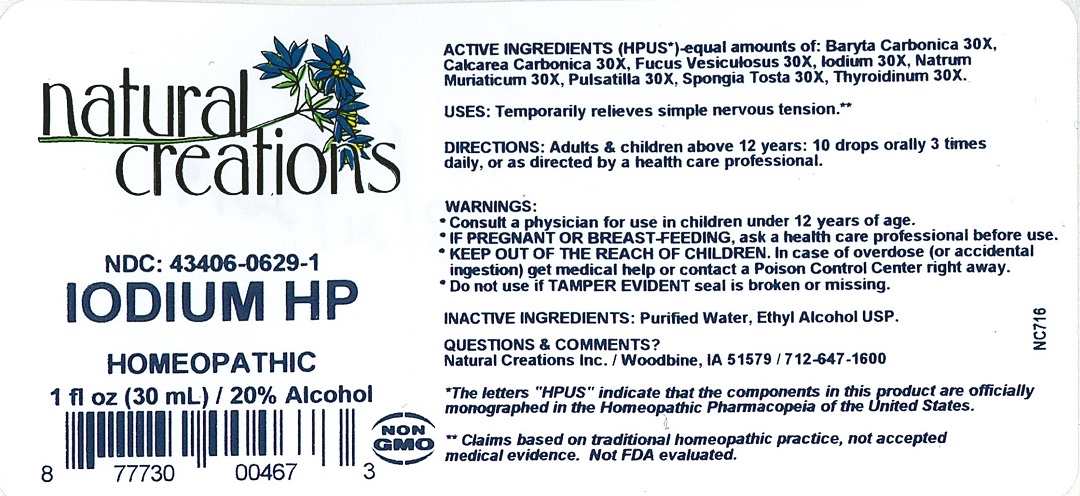 DRUG LABEL: IODIUM HP
NDC: 43406-0629 | Form: LIQUID
Manufacturer: Natural Creations, Inc.
Category: homeopathic | Type: HUMAN OTC DRUG LABEL
Date: 20251216

ACTIVE INGREDIENTS: BARIUM CARBONATE 30 [hp_X]/1 mL; OYSTER SHELL CALCIUM CARBONATE, CRUDE 30 [hp_X]/1 mL; FUCUS VESICULOSUS 30 [hp_X]/1 mL; IODINE 30 [hp_X]/1 mL; SODIUM CHLORIDE 30 [hp_X]/1 mL; PULSATILLA VULGARIS 30 [hp_X]/1 mL; SPONGIA OFFICINALIS SKELETON, ROASTED 30 [hp_X]/1 mL; THYROID, UNSPECIFIED 30 [hp_X]/1 mL
INACTIVE INGREDIENTS: WATER; ALCOHOL

IODIUM HP

ACTIVE INGREDIENT

Active Ingredients (HPUS*) - equal amounts of: Baryta Carbonica 30X, Calcarea Carbonica 30X, Fucus Vesiculosus 30X, Iodium 30X, Natrum Muriaticum 30X, Pulsatilla 30X, Spongia Tosta 30X, Thyroidinum 30X

INDICATIONS AND USAGE

USES: Temporarily relieves simple nervous tension.**

WARNING:

- Consult a physician for use in children under 12 years of age.
- IF PREGNANT OR BREAST-FEEDING, ask a health care professional before use.
- KEEP OUT OF THE REACH OF CHILDREN. In case of overdose (or accidental ingestion) get medical help or contact a Poison Control Center right away.
- Do not use if TAMPER EVIDENT seal is broken or missing.

DOSAGE AND ADMINISTRATION

DIRECTIONS: Adults and children above 12 years: 10 drops orally 3 times daily, or as directed by a health care professional.

REFERENCES

*The letters "HPUS" indicate the components in the product are officially monographed in the Homeopathic Pharmacopeia of the United States.

**Claims based on traditional homeopathic practice, not accepted medical evidence. Not FDA evaluated.

INACTIVE INGREDIENTS: Ethyl Alcohol USP, Purified Water.

QUESTIONS AND COMMENTS?

Natural Creations, Inc. / Woodbine, IA 51579 / 712-647-1600

PURPOSE

USES: Temporarily relieves simple nervous tension.**

KEEP OUT OF REACH OF CHILDREN

KEEP OUT OF THE REACH OF CHILDREN. In case of overdose (or accidental ingestion) get medical help or contact a Poison Control Center.

PACKAGE LABEL

NDC: 43406-0629-1

IODIUM HP

HOMEOPATHIC

1 fl oz (30 mL) / 20% Alcohol

UPC: 877730004673 NON GMO Logo